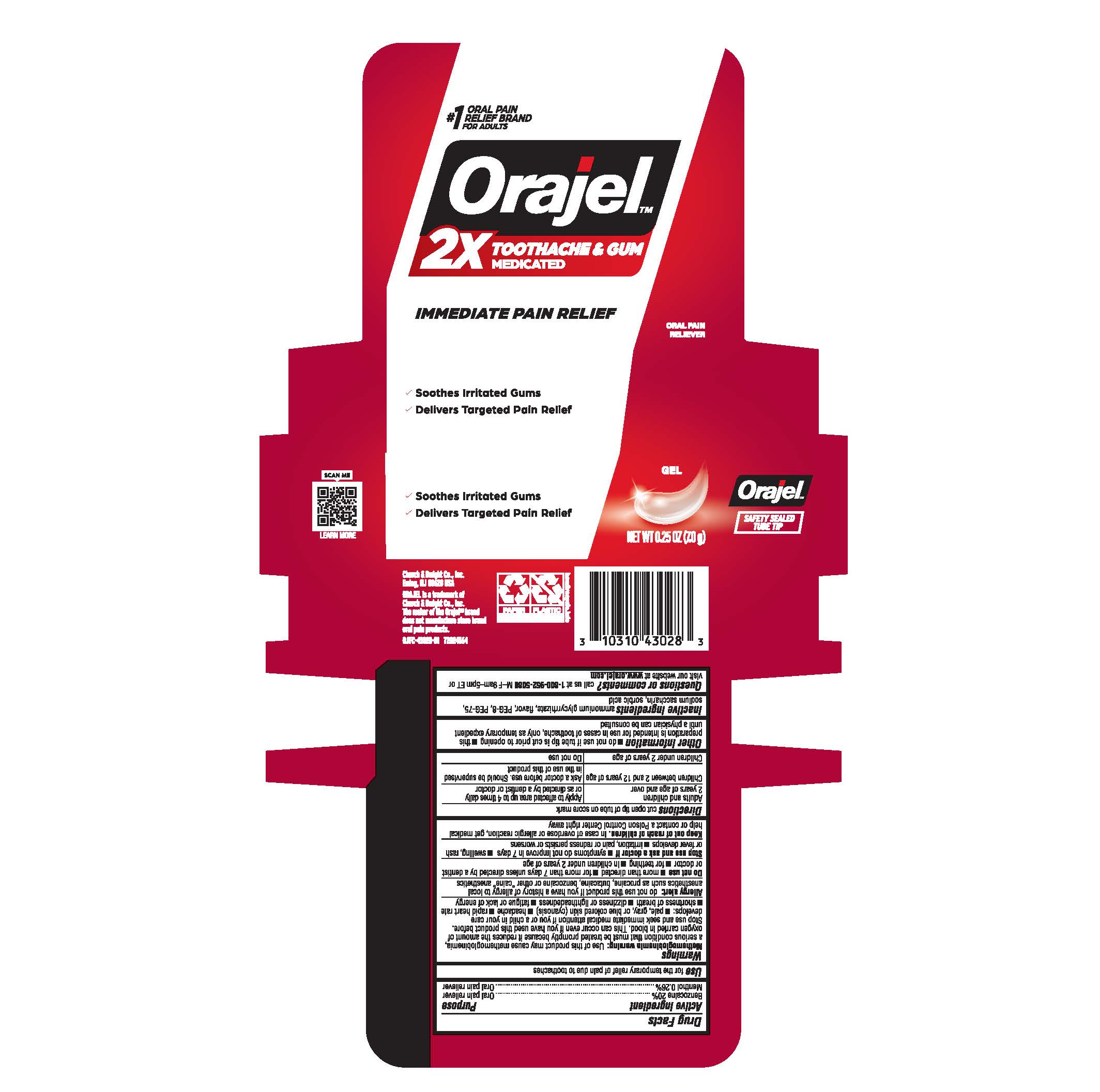 DRUG LABEL: Orajel 2X Medicated Gel
NDC: 10237-782 | Form: GEL
Manufacturer: Church & Dwight Co., Inc.
Category: otc | Type: HUMAN OTC DRUG LABEL
Date: 20241105

ACTIVE INGREDIENTS: BENZOCAINE 200 mg/1 g; MENTHOL 2.6 mg/1 g
INACTIVE INGREDIENTS: POLYETHYLENE GLYCOL 400; AMMONIUM GLYCYRRHIZATE; SODIUM SACCHARIN; POLYETHYLENE GLYCOL 3350; SORBIC ACID

ACTIVE INGREDIENT

Benzocaine 20%

Menthol 0.26%

PURPOSE

Oral pain reliever

USE

for the temporary relief of pain due to toothaches

WARNINGS

Methemogloblnemla warning: Use of this product may cause methemoglobinemia,
a serious condition that must be treated promptly because it reduces the amount of
oxygen carried in blood. This can occur even if you have used this product before.
Stop use and seek immediate medical attention if you or a child in your care
develops: ■ pale, gray, or blue colored skin (cyanosis) ■ headache ■ rapid heart rate
■ shortness of breath ■ dizziness or lightheadedness ■ fatigue or lack of energy

Allergy alert: do not use this product if you have a history of allergy to local
anesthetics such as procaine, butacalne, benzocaine or other "caine" anesthetics

Do not use ■ more than directed ■ for more than 7 days unless directed by a dentist
or doctor ■ for teething ■ in children under 2 years of age

Stop use and ask a doctor if ■ symptoms do not improve in 7 days ■ swelling, rash
or fever develops ■ irrnation, pain or redness persists or worsens

Keep out of reach of children. In case of overdose or allergic reaction, get medical
help or contact a Poison Control Center right away

DIRECTIONS

- cut open tip of tube on score mark

Adults and children 2 years of age and over: apply to affected area up to 4 times daily or as directed by a dentist or doctor

Children between 2 and 12 years of age: ask a doctor before use. Should be supervised in the use of this product.
Children under 2 years of age: do not use

Other information

■ do not use if tube tip is cut prior to opening ■ this preparation is intended for use in cases of toothache, only as temporary expedient
until a physician can be consulted

Inactive ingredients

ammonium glycyrrhizate, flavor, PEG-8, PEG-75, sodium saccharin, sorbic acid

Questions or comments?

call us at 1-800-952-5080 M-F 9am-5pm ET or visit our website at www.orajel.com

PACKAGE LABEL

#1 ORAL PAIN RELIEF BRAND FOR ADULTS

ORAJELTM

2X TOOTHACHE & GUM MEDICATED

IMMEDIATE PAIN RELIEF

ORAL PAIN RELIEVER

- Soothes Irritated Gums
- Delivers Targeted Pain Relief

GEL

NET WT 0.25 OZ (7.0 g)